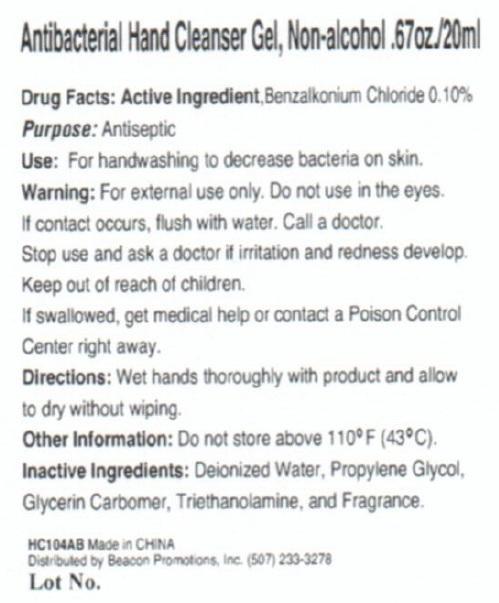 DRUG LABEL: Antibacterial Hand Cleanser, Non-Alcohol
NDC: 75866-001 | Form: GEL
Manufacturer: Beacon Promotions
Category: otc | Type: HUMAN OTC DRUG LABEL
Date: 20140220

ACTIVE INGREDIENTS: BENZALKONIUM CHLORIDE 1.0 mg/1 mL
INACTIVE INGREDIENTS: WATER; PROPYLENE GLYCOL; GLYCERIN; TROLAMINE

Antibacterial Hand Cleanser Gel, Non-alcohol

Drug Facts:

Active Ingredient, Benzalkonium Chloride 0.10%

Purpose:

Antiseptic

INDICATIONS AND USAGE

Use: For handwashing to decrease bacteria on skin.

WARNINGS

Warning: For external use only. Do not use in the eyes. If contact occurs, flush with water. Call a doctor

Stop use and ask a doctor if irritation and redness develop

keep out of reach of children

If swallowed, get medical help or contact a Poison Control Center right away

Directions

Wet hands thoroughly with product and allow to dry without wiping.

STORAGE AND HANDLING

Do not store above 100degrees F (43degrees C)

INACTIVE INGREDIENT

Deionized water, Propylene Glycol, Glycerin Carbomer, Triethanolamine, and Fragrance

HC104AB Made in China

Distributed by Beacon Promotions, Inc.

(507) 233-3278

Lot No.